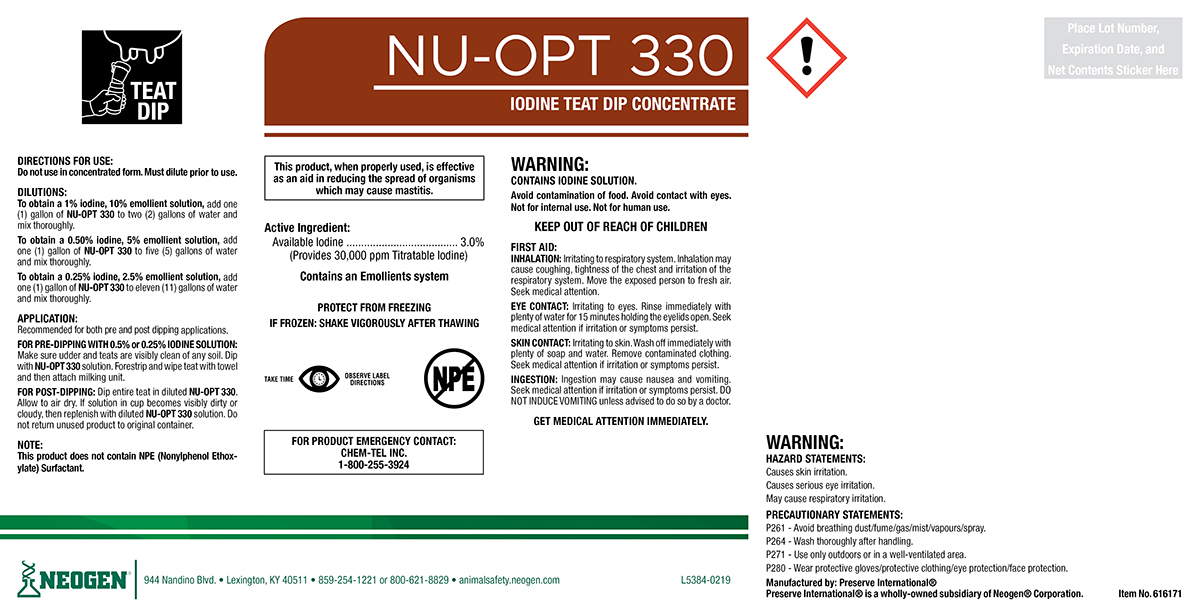 DRUG LABEL: NU-OPT 330
NDC: 60648-9014 | Form: SOLUTION
Manufacturer: Preserve International
Category: animal | Type: OTC ANIMAL DRUG LABEL
Date: 20190521

ACTIVE INGREDIENTS: IODINE 33.36 g/1 L

NU-OPT 330

DIRECTIONS FOR USE:

Do not use in concentrated form. Must dilute prior to use.

DIRECTIONS:

To obtain a 1% Iodine, 10% emollient solution, add one (1) gallon of NU-OPT 330 to two (2) gallons of water and mix thoroughly.

To obtain a 0.50% Iodine, 5% emollient solution, add one (1) gallon of NU-OPT 330 to five (5) gallons of water and mix thoroughly.

To obtain a 0.25% Iodine, 2.5% emollient solution, add one (1) gallon of NU-OPT 330 to eleven (11) gallons of water and mix thoroughly.

APPLICATION:

Recommended for both pre and post dipping applications.

FOR PRE-DIPPING WITH 0.5% OR 0.25% IODINE SOLUTION: Make sure udder and teats are visibly clean of any soil. Dip with NU-OPT 330 solution. Forestrip and wipe teat with towel and then attach milking unit.

FOR POST-DIPPING: Dip Entire teat in diluted NU-OPT 330. Allow to air dry. If solution in cup becomes visibly dirty or cloudy, then replenish with diluted NU-OPT 330 solution. Do not return unused product to original container.

NOTE:

This product does not contain NPE (Nonylphenol Ethoxylate) Surfactant.

WARNINGS AND PRECAUTIONS

PROTECT FROM FREEZING

IF FROZEN: SHAKE VIGOROUSLY AFTER THAWING

WARNINGS AND PRECAUTIONS

TAKE TIME OBSERVE LABEL DIRECTIONS

WARNING:

CONTAINS IODINE SOLUTION.

Avoid contamination of food. Avoid contact with eyes. Not for internal use. Not for human use.

KEEP OUT OF REACH OF CHILDREN

FIRST AID:

INHALATION: Irritating to respiratory system. Inhalation may cause coughing, tightness of the chest and irritation of the respiratory system. Move the exposed person to fresh air. Seek medical attention.

EYECONTACT: Irritating to the eyes. Rinse immediately with plenty of water for 15 minutes holding te eyelids open. Seek medical attention if irritation or symptoms persist.

SKIN CONTACT: Irritating to skin. Wash off immediately with plenty of soap and water. Remove contaminated clothing. Seek medical attention if irritation or symptoms persist.

INGESTION: Ingestion may cause nausea and vomiting. Seek medical attention if irritation or symptoms persist. DO NOT INDUCE VOMITING unless advised to do so by a doctor.
GET MEDICAL ATTENTION IMMEDIATELY.

FOR PRODUCT EMERGENCY CONTACT: Chem-Tel Inc. 1-800-255-3924

HAZARD STATEMENTS:

Causes skin irritation.

Causes serious eye irritation.

May cause respiratory irritation.

PRECAUSTIONARY STATEMENTS:

P261 - Avoid breathing dust/fume/gas/mist/vapours/spray.

P264 - Wash thoroughly after handling.

P271 - Use only outdoors or in a well-ventilated area.

P280 - Wear protective gloves/protective clothing/eye protection/face protection.

PACKAGE LABEL

NU-OPT 330

IODINE TEAT DIP CONCENTRATE

This product, when properly used, is effective as an aid
in reducing the spread of organisms which may cause
mastitis.

Active Ingredient

Available Iodine..........3.00% (provides 30,000 ppm Titratable Iodine)
Contains an Emollients system

Manufactured By: Preserve International®

Preserve International® is a wholly-owned subsidiary of Neogen® Corporation.

NEOGEN®

944 Nandino Blvd.

Lexington, KY 40511

859-254-1221 or 800-621-8829

animalsafety.neogen.com